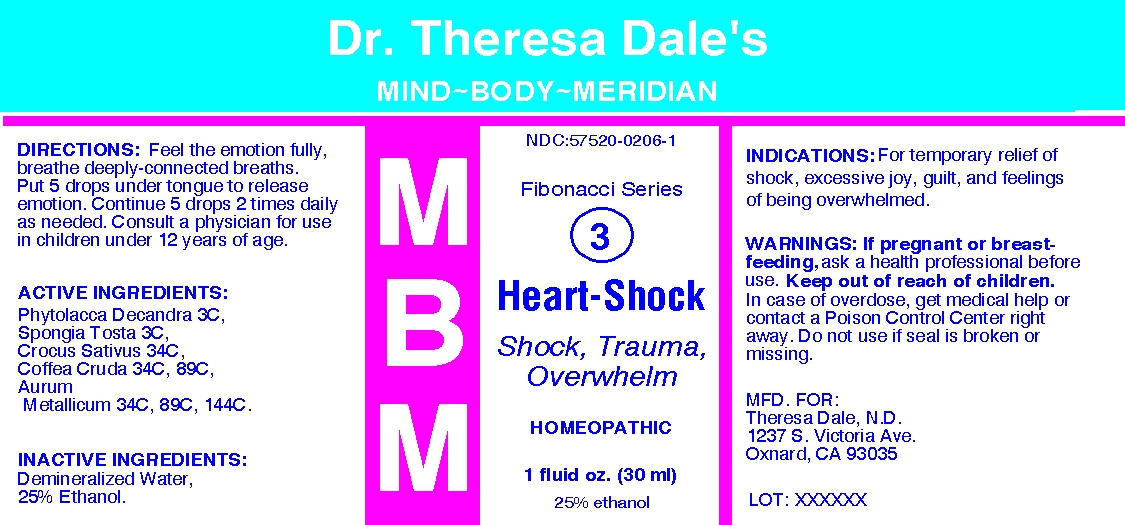 DRUG LABEL: MBM 3 Heart Shock
NDC: 57520-0206 | Form: LIQUID
Manufacturer: Apotheca Company
Category: homeopathic | Type: HUMAN OTC DRUG LABEL
Date: 20100723

ACTIVE INGREDIENTS: PHYTOLACCA AMERICANA ROOT 3 [hp_C]/1 mL; SPONGIA OFFICINALIS SKELETON, ROASTED 3 [hp_C]/1 mL; SAFFRON 34 [hp_C]/1 mL; ARABICA COFFEE BEAN 89 [hp_C]/1 mL; GOLD 144 [hp_C]/1 mL
INACTIVE INGREDIENTS: WATER; ALCOHOL

MBM 3 Heart Shock

ACTIVE INGREDIENT

ACTIVE INGREDIENTS: Phytolacca decandra 3C, Spongia tosta 3C, Crocus sativus 34C, Coffea cruda 34C, 89C, Aurum metallicum 34C, 89C, 144C.

PURPOSE

INDICATIONS: For temporary relief of shock, excessive joy, guilt, and feelings of being overwhelmed.

WARNINGS

WARNINGS: If pregnant or breast-feeding, ask a health professional before use.

Keep out of reach of children. In case of overdose, get medical help or contact a Poison Control Center right away.

Do not use if seal is broken or missing.

DOSAGE AND ADMINISTRATION

DIRECTIONS: Feel the emotion fully, breathe deeply-connected breaths. Put 5 drops under tongue to release emotion. Continue 5 drops 2 times daily as needed. Consult a physician for use in children under 12 years of age.

INACTIVE INGREDIENTS: Demineralized water, 25% Ethanol

QUESTIONS

MFD. FOR:

Theresa Dale, N.D.

1237 S. Victoria Ave.

Oxnard, CA 93035

PACKAGE LABEL

Dr. Theresa Dale's

MIND-BODY-MERIDIAN

Fibonacci Series

3

HEART-SHOCK

Shock, Trauma, Overwhelm

HOMEOPATHIC

1FLUID OZ. (30 ML)